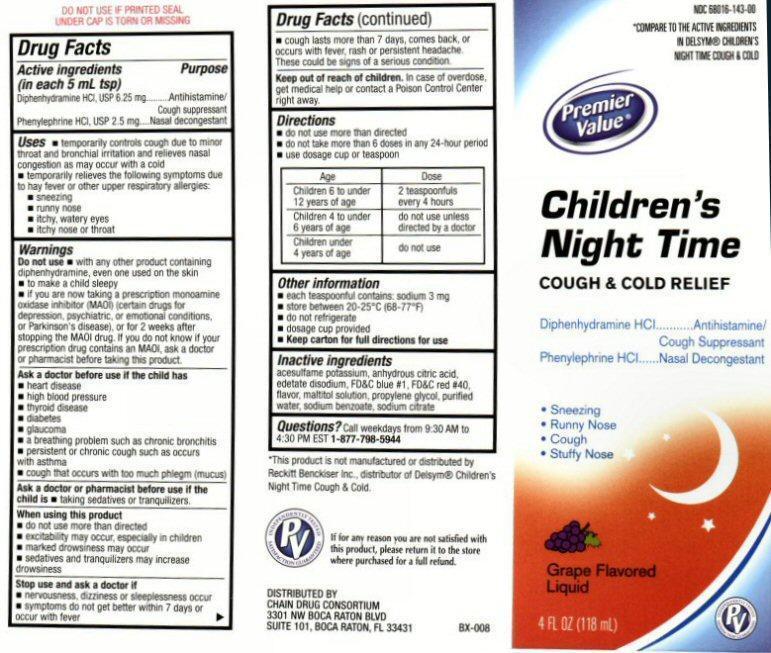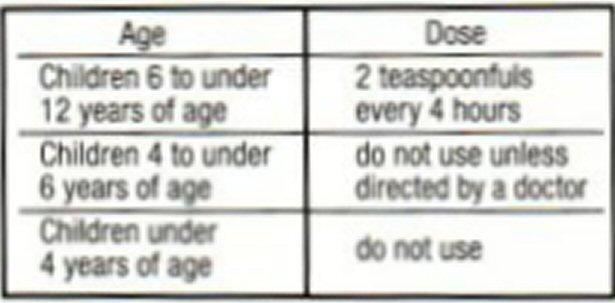 DRUG LABEL: Childrens Night Time
NDC: 68016-143 | Form: LIQUID
Manufacturer: Chain Drug Consortium, LLC
Category: otc | Type: HUMAN OTC DRUG LABEL
Date: 20130401

ACTIVE INGREDIENTS: DIPHENHYDRAMINE HYDROCHLORIDE 6.25 mg/5 mL; PHENYLEPHRINE HYDROCHLORIDE 2.5 mg/5 mL
INACTIVE INGREDIENTS: ACESULFAME POTASSIUM; ANHYDROUS CITRIC ACID; EDETATE DISODIUM; FD&C BLUE NO. 1; FD&C RED NO. 40; MALTITOL; PROPYLENE GLYCOL; WATER; SODIUM BENZOATE; SODIUM CITRATE

Active ingredients

Drug Facts
Active ingredients
(in each 5 mL tsp)
Diphenhydramine HCL,USP 6.25 mg
Phenylephrine HCL, USP 2.5 mg

Purpose

Antihistamine / Cough Suppressant
Nasal Decongestant

Keep out of reach of children

In case of overdose, get medical help or contact a Poison Control center right away.

Uses

- temporarily controls cough due to minor throat and bronchial irritation and relieves nasal congestion as may occur with a cold
- temporarily relieves the following symptoms due to hay fever or other upper respiratory allergies:

- sneezing
- runny nose
- itchy, watery eyes
- itchy nose or throat

Warnings

Do not use

- with any other product containing diphenhydramine, even one used on the skin
- to make a child sleepy
- If you are now taking a prescription monoamine oxidase inhibitor (MAOI) (certain drugs for depression, psychiatric or emotional conditions, or Parkinson’s disease), or for two weeks after stopping the MAOI drug. If you do not know if your child’s prescription drug contains an MAOI, ask a doctor or a pharmacist before taking this product.

Ask a doctor before use if the child has

- heart disease
- high blood pressure
- thyroid disease
- diabetes
- glaucoma
- a breathing problem such as chronic bronchitis
- persistent or chronic cough such as occurs with asthma
- cough that occurs with too much phlegm (mucus)

Ask a doctor or pharmacist before use if the child is

- taking sedatives or tranquilizers.

When using this product

- do not use more than directed
- excitability may occur, especially in children
- marked drowsiness may occur
- sedatives and tranquilizers may increase drowsiness

Stop use and ask a doctor if

- nervousness, dizziness or sleeplessness occus
- symptoms do not get better within 7 days or occur with fever
- cough lasts more than 7 days, comes back, or occurs with fever, rash, or persistent headache.

These could be signs of a serious condition.

Directions

- do not use more than directed
- do not take more than 6 doses in any 24-hour period
- use dosage cup or teaspoon

Other information

- each teaspoonful contains: sodium 3 mg
- store between 20-25 ° C (68-77° F)
- do not refrigerate
- dosage cup provided
- Keep carton for full directions for use

Inactive ingredients

acesulfame potassium, citric acid anhydrous, edeate disodium, FD and C blue #1, FD and C red # 40, flavors, maltitol solution, propylene glycol, purified water, sodium benzoate, sodium citrate

Questions?

Call weekdays from 9:30 AM to 4:30 PM EST at
1-877-798-5944

Product Label

NDC 68016-143-00
*COMPARE TO THE ACTIVE INGREDIENTS IN DELSYM® CHILDREN'S NIGHT TIME COUGH and COLD
Premier Value®
Children's Night Time

COUGH and COLD RELIEF
Diphenhydramine HCL..........Antihistamine / Cough Suppressant
Phenylephrine HCL ............ Nasal Decongestant
Sneezing
Runny Nose
Cough
Stuffy Nose

Grape Flavored Liquid
4 FL OZ (118mL)
INDEPENDENTLY TESTED SATISFACTION GUARANTEED PV
DO NOT USE IF PRINTED SEAL UNDER CAP IS TORN OR MISSING
*This product is not manufactured or distributed by Reckitt Benckiser Inc. distributor of Delsym® Children's Night Time Cough and Cold
If for Any reason you are not satisfied with this product, lease return it to the store where purchased for a full refund.

DISTRIBUTED BY
CHAIN DRUG CONSORTIUM
3301 NW BOCA RATON BLVD
SUITE 101, BOCA RATON, FL 33431
BX-008